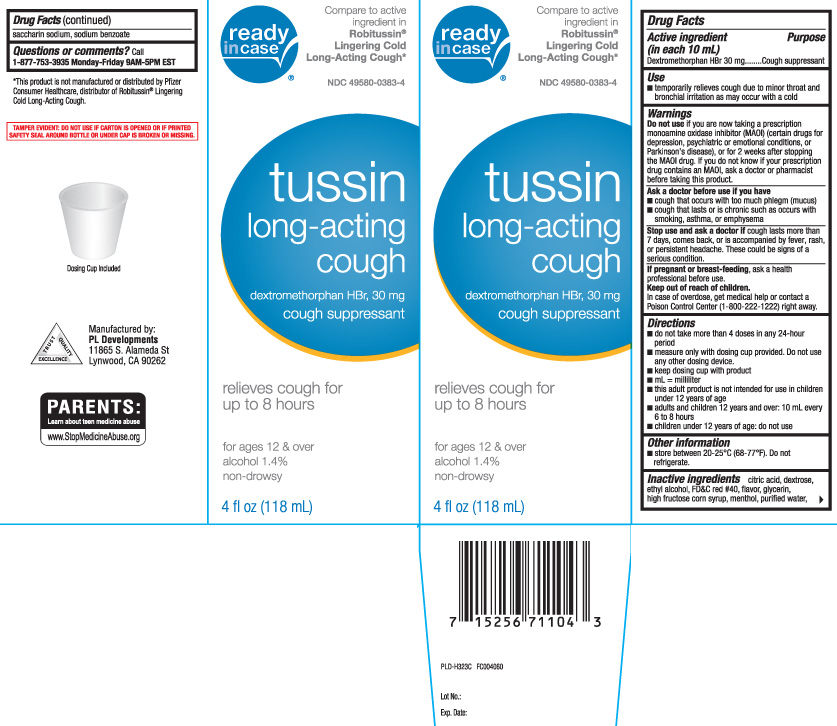 DRUG LABEL: Tussin Long Acting Cough
NDC: 49580-0383 | Form: LIQUID
Manufacturer: P & L Development, LLC
Category: otc | Type: HUMAN OTC DRUG LABEL
Date: 20241210

ACTIVE INGREDIENTS: DEXTROMETHORPHAN HYDROBROMIDE 30 mg/10 mL
INACTIVE INGREDIENTS: ANHYDROUS CITRIC ACID; FD&C RED NO. 40; GLYCERIN; WATER; SODIUM BENZOATE; MENTHOL; ALCOHOL; DEXTROSE; HIGH FRUCTOSE CORN SYRUP; SACCHARIN SODIUM

Drug Facts

Active ingredient (in each 10 mL)

Dextromethorphan HBr, 30 mg

Purpose

Cough suppressant

Uses

- temporarily relieves cough due to minor throat and bronchial irritation as may occur with a cold

Warnings

Do not use

if you are now taking a prescription monoamine oxidase inhibitor (MAOI) (certain drugs for depression, psychiatric, or emotional conditions, or Parkinson’s disease), or for 2 weeks after stopping the MAOI drug. If you do not know if your prescription drug contains an MAOI, ask a doctor or pharmacist before taking this product.

Ask a doctor before use if you have

- cough that occurs with too much phlegm (mucus)
- cough that lasts or is chronic such as occurs with smoking, asthma, or emphysema

Stop use and ask a doctor if

cough lasts more than 7 days, comes back, or is accompanied by fever, rash, or persistent headache. These could be signs of a serious condition.

If pregnant or breast-feeding,

ask a health professional before use.

Keep out of reach of children.

In case of overdose, get medical help or contact a Poison Control Center (1-800-222-1222) right away.

Directions

- do not take more than 4 doses in any 24-hour period
- measure only with dosing cup provided. Do not use any other dosing device.
- keep dosing cup with product
- mL = milliliter
- this adult product is not intended for use in children under 12 years of age
- adults and children 12 years and over: 10 mL every 6 to 8 hours
- children under 12 years: do not use

Other information

- store between 20-25ºC (68-77ºF). Do not refrigerate.

Inactive ingredients

anhydrous citric acid, dextrose, ethyl alcohol, FD&C red 40, flavor, glycerin, high fructose corn syrup, menthol, purified water, saccharin sodium, sodium benzoate

Questions or comments?

Call 1-877-753-3935 Monday-Friday 9AM-5PM EST

Principal Display Panel

Compare to active ingredient in Robitussin® Lingering Cold Long-Acting Cough*

Tussin

Long-acting

Cough

Dextromethorphan HBr, 30 mg

cough suppressant

Relieves cough for up to 8 hours

For ages 12 & over

alcohol 1.4%

non-drowsy

Dosing Cup Included

FL OZ (mL)

*This product is not manufactured or distributed by Pfizer Consumer Healthcare, distributors of Robitussin® Lingering Cold Long-Acting Cough.

TAMPER EVIDENT: DO NOT USE IF CARTON IS OPENED OR IF PRINTED SAFETY SEAL AROUND BOTTLE OR UNDER CAP IS BROKEN OR MISSING.

Manufactured by:

PL Developments

11865 S. Alamea St

Lynwood, CA 90262

Package Label

READYINCASE Tussin long-acting cough